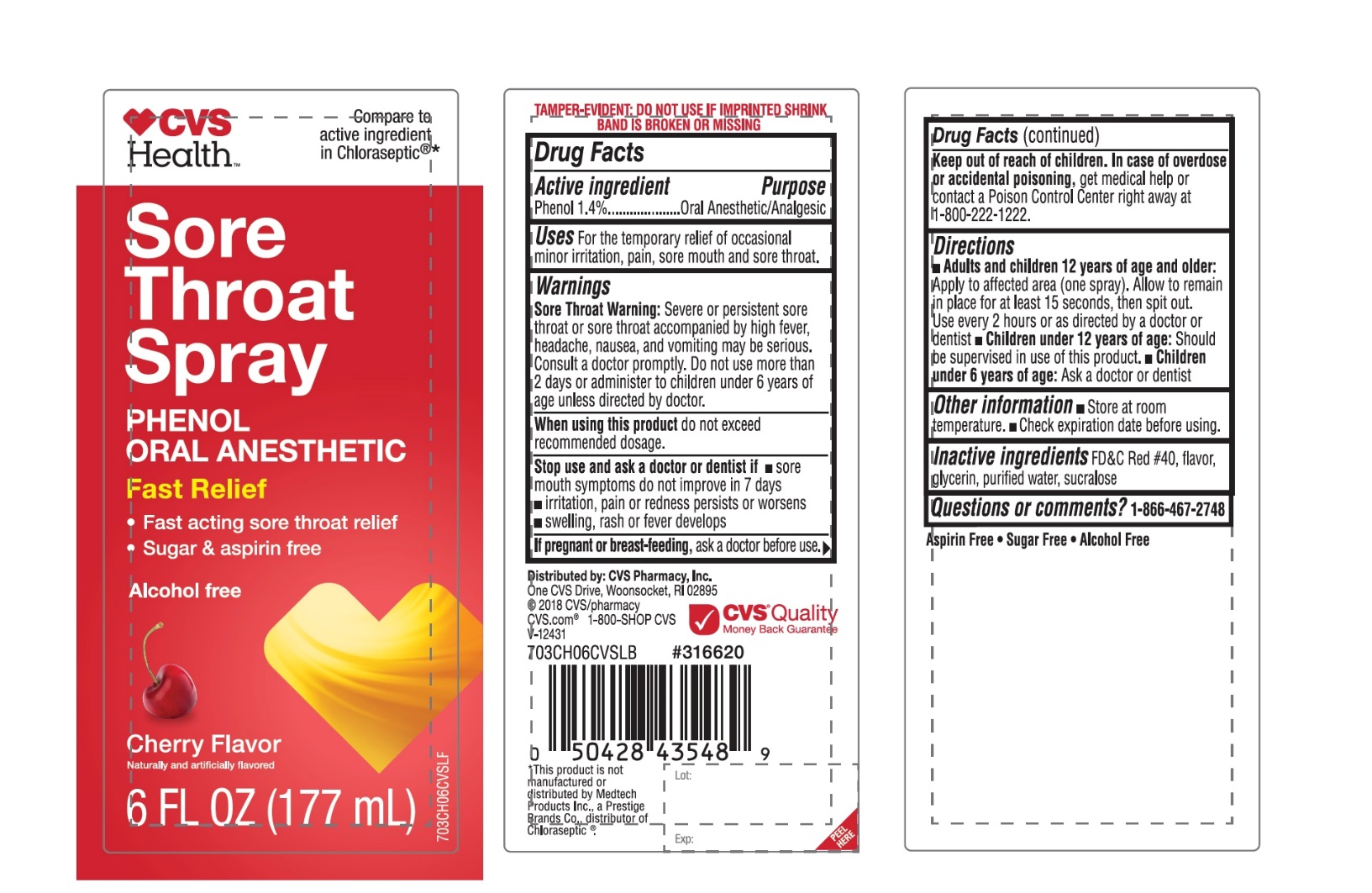 DRUG LABEL: CVS Health Sore Throat Fast Relief Oral Anesthetic
NDC: 59779-895 | Form: SPRAY
Manufacturer: CVS Pharmacy,Inc.
Category: otc | Type: HUMAN OTC DRUG LABEL
Date: 20251209

ACTIVE INGREDIENTS: PHENOL 1.4 g/100 mL
INACTIVE INGREDIENTS: FD&C RED NO. 40; GLYCERIN; WATER; SUCRALOSE

CVS Health Sore Throat Spray Cherry Flavor 6 FL OZ

Active ingredient

Phenol 1.4%

Purpose

Oral Anesthetic/Analgesic

Uses

For the temporary relief of occasional minor irritation, pain, sore mouth and sore throat.

Warnings

Sore Throat Warning:Severe or persistent sore throat or sore throat accompanied by high fever, headache, nausea, and vomiting may be serious.

Consult doctor promptly. Do not use more than 2 days or administer to children under 6 years of age unless directed by doctor.

When using this product,

do not exceed recommended dosage.

Stop use and ask a doctor or dentist if

- sore mouth symptoms do not improve in 7 days
- irritation, pain or redness persists or worsens
- swelling, rash or fever develops

If pregnant or breast-feeding,

ask a doctor before use.

Keep out of reach of children.

In case of overdose or accidental poisoning,get medical help or contact a Poison Control Center right away (1-800-222-1222).

Directions

- Adults and children 6 years of age and older:

- Apply to the affected area (one spray)
- Allow to remain in place for at least 15 seconds, then spit out
- Use every 2 hours or as directed by a doctor or dentist
- Children under 12 years of ageshould be supervised in the use of this product
- Children under 6 years of age:consult a doctor or dentist

Other information

- Store at room temperature
- Check expiration date before using

Inactive ingredients

FD&C Red #40, flavor, glycerin, purified water, sucralose

Questions or comments?

1-866-467-2748

- Aspirin-Free● Sugar-Free ●Gluten-Free ●Alcohol-Free

Principal Display Panel

CVS Health™

*Compare to active ingredient in Chloraseptic®*

Sore Throat Spray

PHENOL ORAL ANESTHETIC

Fast Relief

- Fast acting sore throat relief
- Sugar, gluten & aspirin free
- Alcohol-Free

Cherry Flavor

Naturally and Artificially Flavored

6 FL OZ (177 mL)

*This product is not manufactured or distributed by Medtech Products Inc., a Prestige Brands Co., distributor of Chloraseptic®

TAMPER-EVIDENT: DO NOT USE IF IMPRINTED SHRINK BAND IS BROKEN OR MISSING.

Distributed by: CVS Pharmacy, Inc.

One CVS Drive, Woonsocket, RI 02895

©2018 CVS /Pharmacy

CVS.com 1-800-SHOP CVS

Made in the U.S.A. V-12431

CVS Quality

Money back Guarantee